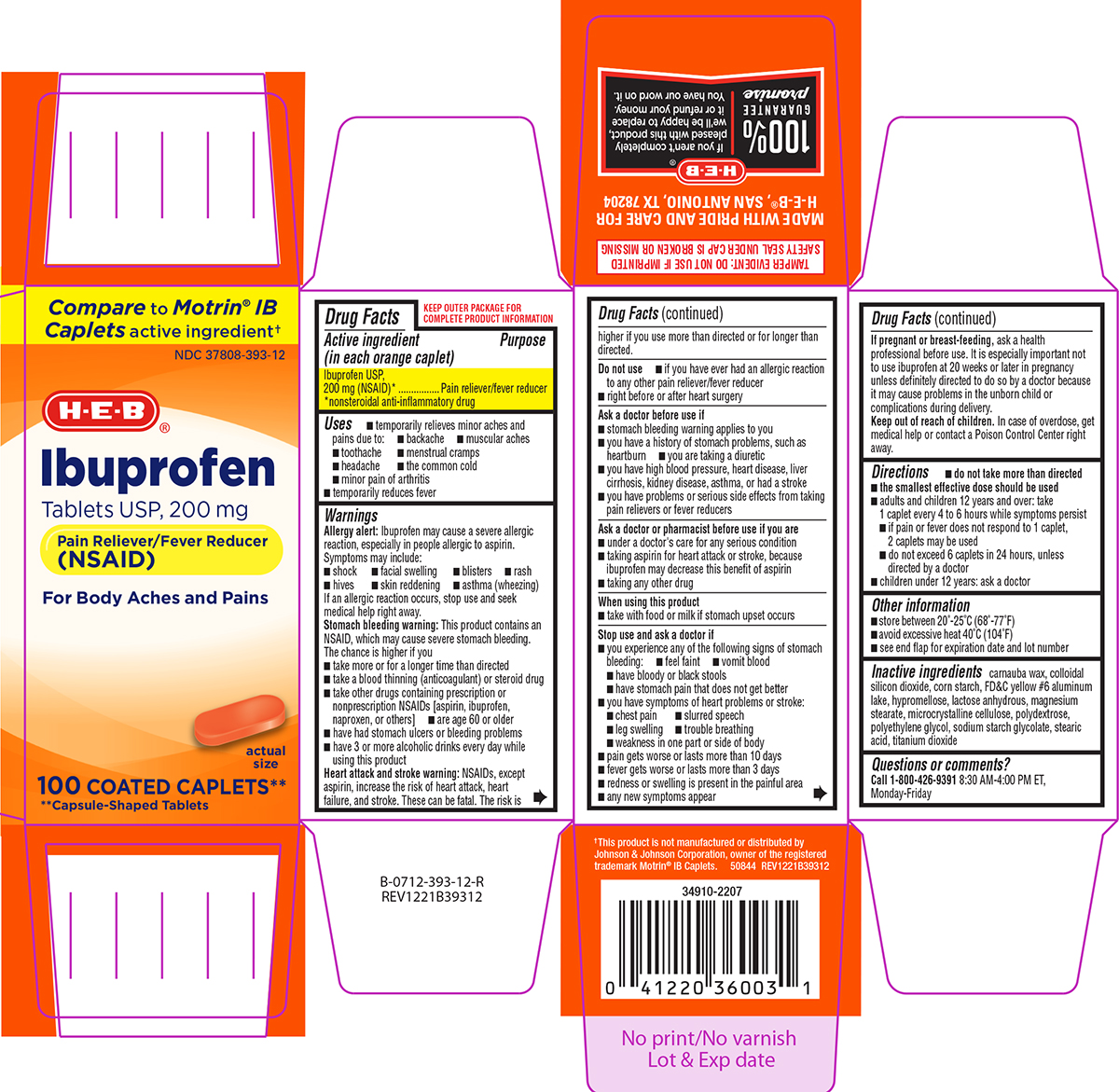 DRUG LABEL: Ibuprofen
NDC: 37808-393 | Form: TABLET, FILM COATED
Manufacturer: H E B
Category: otc | Type: HUMAN OTC DRUG LABEL
Date: 20260202

ACTIVE INGREDIENTS: IBUPROFEN 200 mg/1 1
INACTIVE INGREDIENTS: CARNAUBA WAX; SILICON DIOXIDE; STARCH, CORN; FD&C YELLOW NO. 6 ALUMINUM LAKE; HYPROMELLOSE, UNSPECIFIED; ANHYDROUS LACTOSE; MAGNESIUM STEARATE; MICROCRYSTALLINE CELLULOSE; POLYDEXTROSE; POLYETHYLENE GLYCOL, UNSPECIFIED; SODIUM STARCH GLYCOLATE TYPE A POTATO; STEARIC ACID; TITANIUM DIOXIDE

Ibuprofen

Active ingredient (in each orange caplet)

Ibuprofen USP, 200 mg (NSAID)*
*nonsteroidal anti-inflammatory drug

Purpose

Pain reliever/fever reducer

Uses

- temporarily relieves minor aches and pains due to:
  - headache
  - muscular aches
  - toothache
  - backache
  - menstrual cramps
  - the common cold
  - minor pain of arthritis
- temporarily reduces fever

Warnings

Allergy alert: Ibuprofen may cause a severe allergic reaction, especially in people allergic to aspirin. Symptoms may include:

- rash
- blisters
- hives
- facial swelling
- shock
- asthma (wheezing)
- skin reddening

If an allergic reaction occurs, stop use and seek medical help right away.

Stomach bleeding warning: This product contains an NSAID, which may cause severe stomach bleeding. The chance is higher if you

- are age 60 or older
- have had stomach ulcers or bleeding problems
- take a blood thinning (anticoagulant) or steroid drug
- take other drugs containing prescription or nonprescription NSAIDs [aspirin, ibuprofen, naproxen, or others]
- have 3 or more alcoholic drinks every day while using this product
- take more or for a longer time than directed

Heart attack and stroke warning: NSAIDs, except aspirin, increase the risk of heart attack, heart failure, and stroke. These can be fatal. The risk is higher if you use more than directed or for longer than directed.

Do not use

- if you have ever had an allergic reaction to any other pain reliever/fever reducer
- right before or after heart surgery

Ask a doctor before use if

- you are taking a diuretic
- you have a history of stomach problems, such as heartburn
- stomach bleeding warning applies to you
- you have problems or serious side effects from taking pain relievers or fever reducers
- you have high blood pressure, heart disease, liver cirrhosis, kidney disease, asthma, or had a stroke

Ask a doctor or pharmacist before use if you are

- under a doctor's care for any serious condition
- taking aspirin for heart attack or stroke, because ibuprofen may decrease this benefit of aspirin
- taking any other drug

When using this product

- take with food or milk if stomach upset occurs

Stop use and ask a doctor if

- you experience any of the following signs of stomach bleeding:
  - feel faint
  - vomit blood
  - have bloody or black stools
  - have stomach pain that does not get better
- you have symptoms of heart problems or stroke:
  - chest pain
  - weakness in one part or side of body
  - slurred speech
  - trouble breathing
  - leg swelling
- pain gets worse or lasts more than 10 days
- fever gets worse or lasts more than 3 days
- redness or swelling is present in the painful area
- any new symptoms appear

If pregnant or breast-feeding,

ask a health professional before use. It is especially important not to use ibuprofen at 20 weeks or later in pregnancy unless definitely directed to do so by a doctor because it may cause problems in the unborn child or complications during delivery.

Keep out of reach of children.

In case of overdose, get medical help or contact a Poison Control Center right away.

Directions

- do not take more than directed
- the smallest effective dose should be used
- adults and children 12 years and over: take 1 caplet every 4 to 6 hours while symptoms persist
  - if pain or fever does not respond to 1 caplet, 2 caplets may be used
  - do not exceed 6 caplets in 24 hours, unless directed by a doctor
- children under 12 years: ask a doctor

Other information

- store between 20°-25°C (68°-77°F)
- avoid excessive heat 40°C (104°F)
- see end flap for expiration date and lot number

Inactive ingredients

carnauba wax, colloidal silicon dioxide, corn starch, FD&C yellow #6 aluminum lake, hypromellose, lactose anhydrous, magnesium stearate, microcrystalline cellulose, polydextrose, polyethylene glycol, sodium starch glycolate, stearic acid, titanium dioxide

Questions or comments?

Call 1-800-426-9391 8:30 AM-4:00 PM ET, Monday-Friday

Principal Display Panel

Compare to Motrin® IB
Caplets active ingredient†

NDC 37808-393-12

H-E-B®

Ibuprofen
Tablets USP, 200 mg
Pain Reliever/Fever Reducer
(NSAID)

For Body Aches and Pains

actual
size

100 COATED CAPLETS**
**Capsule-Shaped Tablets

TAMPER EVIDENT: DO NOT USE IF IMPRINTED
SAFETY SEAL UNDER CAP IS BROKEN OR MISSING

† This product is not manufactured or distributed by
Johnson & Johnson Corporation, owner of the registered
trademark Motrin® IB Caplets.

50844 REV1221B39312

MADE WITH PRIDE AND CARE FOR
H-E-B®, SAN ANTONIO, TX 78204

H-E-B®
100%
GUARANTEE
promise

If you aren't completely
pleased with this product,
we'll be happy to replace it
or refund your money.
You have our word on it.

HEB 44-393